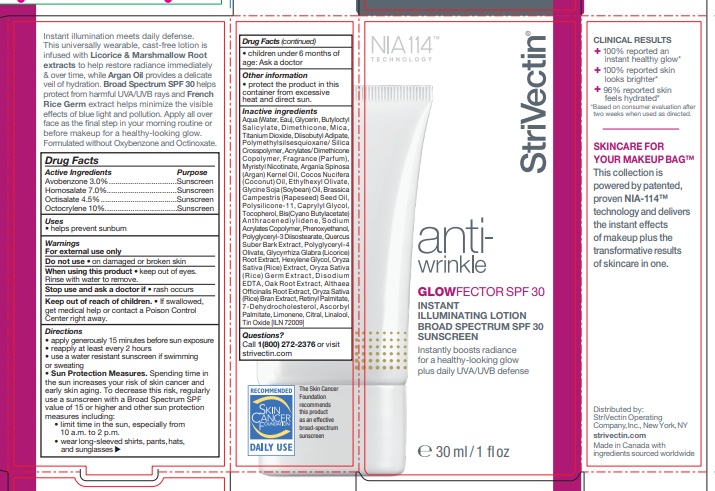 DRUG LABEL: StriVectin ANTI-WRINKLE GLOWFECTOR
NDC: 76147-240 | Form: LOTION
Manufacturer: StriVectin Operating Company, Inc.
Category: otc | Type: HUMAN OTC DRUG LABEL
Date: 20251209

ACTIVE INGREDIENTS: AVOBENZONE 3 g/100 mL; HOMOSALATE 7 g/100 mL; OCTISALATE 4.5 g/100 mL; OCTOCRYLENE 10 g/100 mL
INACTIVE INGREDIENTS: SODIUM ACRYLATES CROSSPOLYMER-2; POLYGLYCERYL-3 DIISOSTEARATE; ETHYLHEXYL OLEATE; DIMETHICONE/VINYL DIMETHICONE CROSSPOLYMER (SOFT PARTICLE); COCONUT OIL; MYRISTYL NICOTINATE; POLYMETHYLSILSESQUIOXANE (4.5 MICRONS); WATER; GLYCERIN; BUTYLOCTYL SALICYLATE; DIMETHICONE; SOYBEAN OIL; MICA; ARGAN OIL; TITANIUM DIOXIDE; DIISOBUTYL ADIPATE; ORYZA SATIVA WHOLE; SILICON DIOXIDE; CANOLA OIL; QUERCUS SUBER BARK; VITAMIN A PALMITATE; LICORICE; 2-ETHYLHEXYL ACRYLATE, METHACRYLATE, METHYL METHACRYLATE, OR BUTYL METHACRYLATE/HYDROXYPROPYL DIMETHICONE COPOLYMER (30000-300000 MW); ASCORBYL PALMITATE; QUERCUS SPP. WHOLE; ALTHAEA OFFICINALIS ROOT; LIMONENE, (+)-; CITRAL; LINALOOL, (+)-; CAPRYLYL GLYCOL; POLYGLYCERYL-4 OLEATE; STANNOUS OXIDE; HEXYLENE GLYCOL; 7-DEHYDROCHOLESTEROL; TOCOPHEROL; ANTHRACENE; PHENOXYETHANOL; EDETATE DISODIUM ANHYDROUS

StriVectin - ANTI-WRINKLE GLOWFECTOR SPF30 (76147-240)

ACTIVE INGREDIENTS

Avobenzone 3.0%
Homosalate 7.0%
Octisalate 4.5%
Octocrylene 10%

PURPOSE

Sunscreen

USES

- helps prevent sunburn
- if used as directed with other sun protection measures (see Directions), decreases the risk of skin cancer and early skin aging caused by the sun

WARNINGS

- For external use only
- Do not use on damaged or broken skin
- When using this product keep out of eyes. Rinse with water to remove.
- Stop use and ask a doctor if rash occurs

- Keep out of reach of children. If swallowed, get medical help or contact a Poison Control Center right away.

DIRECTIONS

- Apply generously 15 minutes before sun exposure
- reapply at least every 2 hours
- use a water resistant sunscreen if swimming or sweating
- Sun Protection Measures. Spending time inthe sun increases your risk of skin cancer andearly skin aging. To decrease this risk, regularly use a sunscreen with a Broad Spectrum SPFvalue of 15 or higher and other sun protectionmeasures including:
- limit time in the sun, especially from 10 a.m. - 2 p.m.
- wear long-sleeved shirts, pants, hats,and sunglasses
- Children under 6 months of age: Ask a doctor

OTHER INFORMATION

Protect the product in this container from excessive heat and direct sun.

INACTIVE INGREDIENTS

Aqua (Water, Eau), Glycerin, Butyloctyl Salicylate, Dimethicone, Mica, Titanium Dioxide, Diisobutyl Adipate, Polymethylsilsesquioxane/ Silica Crosspolymer, Acrylates/ Dimethicone Copolymer, Fragrance (Parfum), Myristyl Nicotinate, Argania Spinosa (Argan) Kernel Oil, Cocos Nucifera (Coconut) Oil, Ethylhexyl Olivate, Glycine Soja (Soybean) Oil, Brassica Campestris (Rapeseed) Seed Oil, Polysilicone-11, Caprylyl Glycol, Tocopherol, Bis(Cyano Butylacetate) Anthracenediylidene, Sodium Acrylates Copolymer, Phenoxyethanol, Polyglyceryl-3 Diisostearate, Quercus Suber Bark Extract, Polyglyceryl-4 Olivate, Glycyrrhiza Glabra (Licorice) Root Extract, Hexylene Glycol, Oryza Sativa (Rice) Extract, Oryza Sativa (Rice) Germ Extract, Disodium EDTA, Oak Root Extract, Althaea Officinalis Root Extract, Oryza Sativa (Rice) Bran Extract, Retinyl Palmitate, 7-Dehydrocholesterol, Ascorbyl Palmitate, Limonene, Citral, Linalool, Tin Oxide